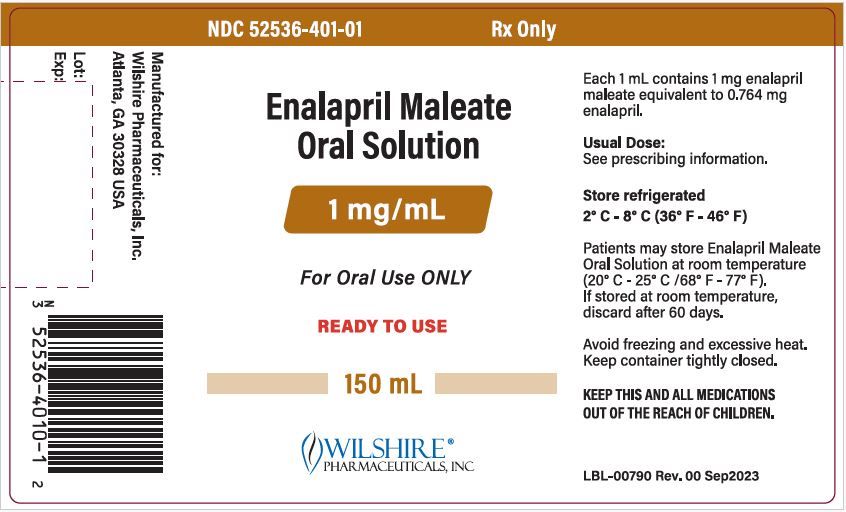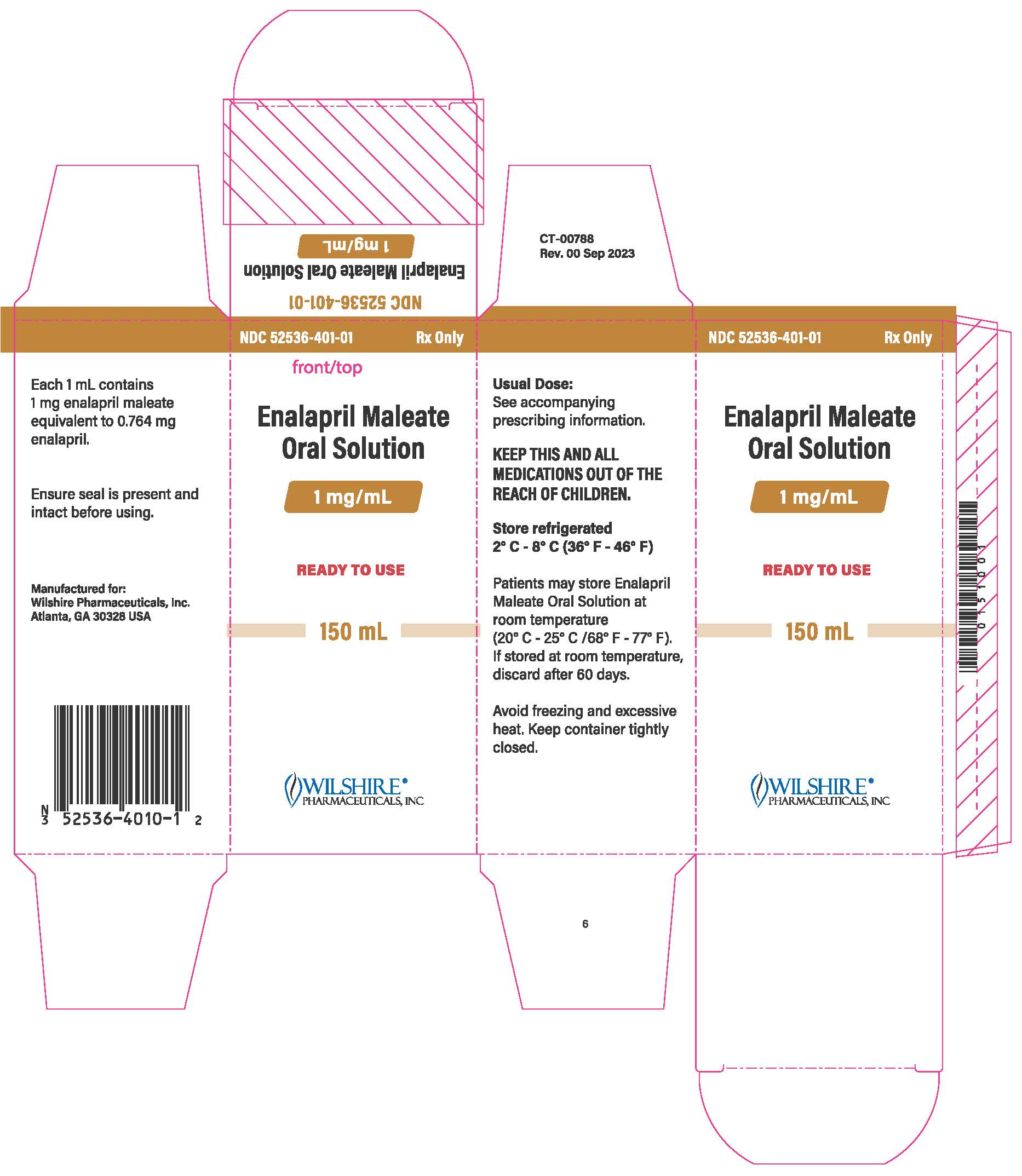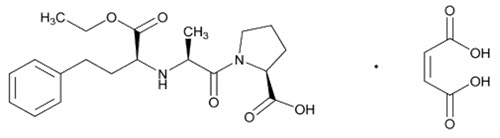 DRUG LABEL: Enalapril maleate
NDC: 52536-401 | Form: SOLUTION
Manufacturer: Wilshire Pharmaceuticals, Inc.
Category: prescription | Type: HUMAN PRESCRIPTION DRUG LABEL
Date: 20251216

ACTIVE INGREDIENTS: ENALAPRIL MALEATE 1 mg/1 mL
INACTIVE INGREDIENTS: CITRIC ACID MONOHYDRATE; WATER; SODIUM BENZOATE; SODIUM CITRATE, UNSPECIFIED FORM; SUCRALOSE; HYDROCHLORIC ACID; SODIUM HYDROXIDE

HIGHLIGHTS OF PRESCRIBING INFORMATION

These highlights do not include all the information needed to use ENALAPRIL MALEATE safely and effectively. See full prescribing information for ENALAPRIL MALEATE.
ENALAPRIL MALEATE oral solution
Initial U.S. Approval: 1985

WARNING: FETAL TOXICITY

See full prescribing information for complete boxed warning.

• When pregnancy is detected, discontinue ENALAPRIL MALEATE as soon as possible (5.1).

• Drugs that act directly on the renin-angiotensin system can cause injury and death to the developing fetus (5.1).

1 INDICATIONS AND USAGE

Enalapril maleate is an angiotensin-converting enzyme inhibitor indicated for:

- treatment of hypertension in adults and children older than one month, to lower blood pressure. Lowering blood pressure reduces the risk of fatal and nonfatal cardiovascular events, primarily strokes and myocardial infarctions (1.1).
- treatment of symptomatic heart failure (1.2).
- treatment of asymptomatic left ventricular dysfunction, to decrease the rate of development of overt heart failure and reduce hospitalization for heart failure (1.3).

2 DOSAGE AND ADMINISTRATION

Hypertension

- Adult: recommended initial dose is 5 mg once daily. Maximum dose is 40 mg daily (2.1).
- Pediatrics: recommended starting dose is 0.08 mg/kg (up to 5 mg) once daily (2.1).

Heart Failure: Initiate at 2.5 mg twice daily. Titrate up to 20 mg twice daily as tolerated (2.2).

Asymptomatic Left Ventricular Dysfunction: Initiate at 2.5 mg twice daily. Titrate up to 10 mg twice daily (2.3).

Enalapril maleate oral solution is a ready-to-use solution intended for oral use only.

3 DOSAGE FORMS AND STRENGTHS

Enalapril maleate oral solution is a ready-to-use oral solution: 1 mg/mL enalapril maleate. (3)

4 CONTRAINDICATIONS

- Hypersensitivity related to previous treatment with an ACEI (4).
- Hereditary or idiopathic angioedema (4).
- Do not co-administer aliskiren in patients with diabetes (4).
- In combination with a neprilysin inhibitor (4).

5 WARNINGS AND PRECAUTIONS

- Angioedema and Anaphylactoid Reactions (5.2).
- Impaired Renal Function: Assess renal function (5.5).
- Hyperkalemia (5.6).

6 ADVERSE REACTIONS

- The most common adverse reaction for patients treated for hypertension (≥3%) was fatigue (6.1).
- The most common adverse reactions for patients treated for heart failure (>6%) were hypotension and dizziness (6.1).

To report SUSPECTED ADVERSE REACTIONS, contact Wilshire Pharmaceuticals, Inc. at 1-877-495-6856 or FDA at 1-800-FDA-1088 or www.fda.gov/medwatch.

7 DRUG INTERACTIONS

- In patients who are elderly, volume-depleted (as on diuretic therapy), or with compromised renal function, use with NSAIDs, including selective COX-2 inhibitors, may result in deterioration of renal function, including renal failure. Monitor renal function periodically (7.1).
- Dual inhibition of the renin-angiotensin system: Increased risk of renal impairment, hypotension and hyperkalemia (7.2).
- Avoid potassium sparing agents in patients with heart failure (7.3).
- Monitor serum lithium levels frequently (7.4).

8 USE IN SPECIFIC POPULATIONS

- Enalapril maleate is not recommended in neonates and in pediatric patients with glomerular filtration rate <30 mL/min/1.73 m^2(8.4).
- Lactation: Advise not to breastfeed (8.2).

FULL PRESCRIBING INFORMATION

WARNING: FETAL TOXICITY

• When pregnancy is detected, discontinue ENALAPRIL MALEATE as soon as possible. [See Warnings and Precautions (5.1)]

• Drugs that act directly on the renin-angiotensin system can cause injury and death to the developing fetus. [See Warnings and Precautions (5.1)]

1 INDICATIONS AND USAGE

1.1 Hypertension

Enalapril maleate is indicated for the treatment of hypertension, to lower blood pressure in adults and children older than one month [see Pediatric Use (8.4) and Clinical Studies (14)].

Lowering blood pressure reduces the risk of fatal and nonfatal cardiovascular events, primarily strokes and myocardial infarctions. These benefits have been seen in controlled trials of antihypertensive drugs from a wide variety of pharmacologic classes including this drug.

Control of high blood pressure should be part of comprehensive cardiovascular risk management, including, as appropriate, lipid control, diabetes management, antithrombotic therapy, smoking cessation, exercise, and limited sodium intake. Many patients will require more than one drug to achieve blood pressure goals. For specific advice on goals and management, see published guidelines, such as those of the National High Blood Pressure Education Program’s Joint National Committee on Prevention, Detection, Evaluation, and Treatment of High Blood Pressure (JNC).

Numerous antihypertensive drugs, from a variety of pharmacologic classes and with different mechanisms of action, have been shown in randomized controlled trials to reduce cardiovascular morbidity and mortality, and it can be concluded that it is blood pressure reduction, and not some other pharmacologic property of the drugs, that is largely responsible for those benefits. The largest and most consistent cardiovascular outcome benefit has been a reduction in the risk of stroke, but reductions in myocardial infarction and cardiovascular mortality also have been seen regularly.

Elevated systolic or diastolic pressure causes increased cardiovascular risk, and the absolute risk increase per mmHg is greater at higher blood pressures, so that even modest reductions of severe hypertension can provide substantial benefit. Relative risk reduction from blood pressure reduction is similar across populations with varying absolute risk, so the absolute benefit is greater in patients who are at higher risk independent of their hypertension (for example, patients with diabetes or hyperlipidemia), and such patients would be expected to benefit from more aggressive treatment to a lower blood pressure goal.

Some antihypertensive drugs have smaller blood pressure effects (as monotherapy) in Black patients, and many antihypertensive drugs have additional approved indications and effects (e.g., on angina, heart failure, or diabetic kidney disease). These considerations may guide selection of therapy.

Enalapril maleate is effective alone or in combination with other antihypertensive agents, especially thiazide-type diuretics. The blood pressure lowering effects of enalapril maleate and thiazides are approximately additive.

1.2 Heart Failure

Enalapril maleate is indicated for the treatment of symptomatic heart failure, usually in combination with diuretics and digitalis. In these patients, enalapril maleate increases survival and decreases the frequency of hospitalization.

1.3 Asymptomatic Left Ventricular Dysfunction

In clinically stable asymptomatic patients with left ventricular dysfunction (ejection fraction ≤35 percent), enalapril maleate decreases the rate of development of overt heart failure and decreases the incidence of hospitalization for heart failure.

2 DOSAGE AND ADMINISTRATION

2.1 Hypertension

Adults:The recommended initial dose in adults is 5 mg taken orally once a day. Titrate upward to maximum of 40 mg daily as needed to help achieve blood pressure goals. The dose may be divided and administered twice daily if the antihypertensive effect diminishes at the end of the dosing interval.

Use with diuretics:If additional blood pressure reduction is needed, enalapril maleate may be administered with a low dose of diuretic. The recommended initial dose in patients taking diuretics is 2.5 mg daily.

Dosage Adjustment for Renal Impairment:See table below. The dosage may be titrated upward as needed to a maximum of 40 mg daily.

Renal Status | Creatinine-Clearance mL/min | Initial Dose mg/day
Normal or Mild Impairment of Renal Function | >30 mL/min | 5 mg
Moderate to Severe Impairment | ≤30 mL/min | 2.5 mg
Dialysis Patients [[See Warnings and Precautions (5.2)] .] [Should be taken after hemodialysis on dialysis days [see Clinical Pharmacology (12.3)] . Calculated using ideal body weight.] | – | 2.5 mg

Children greater than 1 month of age:The usual recommended starting dose is 0.08 mg/kg (up to 5 mg) once daily. Adjust dose based on blood pressure response. Doses above 0.58 mg/kg (or in excess of 40 mg) have not been studied in pediatric patients [see Clinical Pharmacology (12.3)] .

Enalapril maleate is not recommended in neonates (i.e., infants 1 month of age or less), preterm infants who have not reached a corrected post-conceptual age of 44 weeks, and in pediatric patients with glomerular filtration rate <30 mL/min/1.73 m^2.

2.2 Heart Failure

The recommended initial dose is 2.5 mg twice a day titrated up to a maximum of 20 mg twice a day, as tolerated. Doses are usually given in combination with diuretics and digitalis.

In patients with hyponatremia (serum sodium less than 130 mEq/L) or serum creatinine greater than 1.6 mg/dL, the recommended initial dose is 2.5 mg once daily.

Diuretic dose may need to be adjusted to minimize hypovolemia and hypotension. The appearance of hypotension after the initial dose of enalapril maleate does not preclude subsequent careful dose titration with the drug, following effective management of the hypotension.

2.3 Asymptomatic Left Ventricular Dysfunction

The recommended initial dose is 2.5 mg twice a day titrated up to a maximum of 10 mg twice a day, as tolerated. Diuretic dose may need to be adjusted [ see Dosage and Administration (2.1)].

3 DOSAGE FORMS AND STRENGTHS

Enalapril maleate is a ready-to-use oral solution that contains 1 mg/mL of enalapril maleate. It is a clear, colorless solution with a mixed berry flavor packaged in a 150 mL white, round, high-density polyethylene bottle with a white, polypropylene, child-resistant cap and tamper-evident seal. Each bottle contains 150 mL.

4 CONTRAINDICATIONS

Enalapril maleate is contraindicated in patients with:

•a history of angioedema or hypersensitivity related to previous treatment with an angiotensin converting enzyme (ACE) inhibitor [see Warnings and Precautions (5.2)].

•hereditary or idiopathic angioedema [see Warnings and Precautions (5.2)] .

Do not co-administer aliskiren with enalapril maleate in patients with diabetes [see Drug Interactions (7.2)] .

Enalapril maleate is contraindicated in combination with a neprilysin inhibitor (e.g., sacubitril). Do not administer enalapril maleate within 36 hours of switching to or from sacubitril/valsartan, a neprilysin inhibitor [see Warnings and Precautions (5.2)] .

5 WARNINGS AND PRECAUTIONS

5.1 Fetal Toxicity

Use of drugs that act on the renin-angiotensin system during the second and third trimesters of pregnancy reduces fetal renal function and increases fetal and neonatal morbidity and death. Resulting oligohydramnios can be associated with fetal lung hypoplasia and skeletal deformations. Potential neonatal adverse effects include skull hypoplasia, anuria, hypotension, renal failure, and death. When pregnancy is detected, discontinue enalapril maleate as soon as possible [see Usein Specific Populations (8.1)] .

5.2 Angioedema and Anaphylactoid Reactions

Angioedema

Head and Neck Angioedema

Angioedema of the face, extremities, lips, tongue, glottis and/or larynx, including some fatal reactions, have occurred in patients treated with angiotensin converting enzyme inhibitors, including enalapril maleate, at any time during treatment. Patients with involvement of the tongue, glottis or larynx are likely to experience airway obstruction, especially those with a history of airway surgery. Enalapril maleate should be promptly discontinued and appropriate therapy and monitoring should be provided until complete and sustained resolution of signs and symptoms of angioedema has occurred.

Patients with a history of angioedema unrelated to ACE inhibitor therapy may be at increased risk of angioedema while receiving an ACE inhibitor [see Contraindications (4)] . ACE inhibitors have been associated with a higher rate of angioedema in Black than in non-Black patients.

Patients receiving coadministration of ACE inhibitor and mTOR (mammalian target of rapamycin) inhibitor (e.g., temsirolimus, sirolimus, everolimus) therapy or a neprilysin inhibitor may be at increased risk for angioedema [see Drug Interactions (7.6, 7.7)].

Intestinal Angioedema

Intestinal angioedema has occurred in patients treated with ACE inhibitors. These patients presented with abdominal pain (with or without nausea or vomiting); in some cases there was no prior history of facial angioedema and C-1 esterase levels were normal. In some cases, the angioedema was diagnosed by procedures including abdominal CT scan or ultrasound, or at surgery, and symptoms resolved after stopping the ACE inhibitor.

Anaphylactoid Reactions

Anaphylactoid Reactions during Desensitization

Two patients undergoing desensitizing treatment with hymenoptera venom while receiving ACE inhibitors sustained life-threatening anaphylactoid reactions.

Anaphylactoid Reactions during Dialysis

Sudden and potentially life-threatening anaphylactoid reactions have occurred in some patients dialyzed with high-flux membranes and treated concomitantly with an ACE inhibitor. In such patients, dialysis must be stopped immediately, and aggressive therapy for anaphylactoid reactions must be initiated. Symptoms have not been relieved by antihistamines in these situations. In these patients, consideration should be given to using a different type of dialysis membrane or a different class of antihypertensive agent. Anaphylactoid reactions have also been reported in patients undergoing low-density lipoprotein apheresis with dextran sulfate absorption.

5.3 Hypotension

Enalapril maleate can cause symptomatic hypotension, sometimes complicated by oliguria, progressive azotemia, acute renal failure or death. Patients at risk of excessive hypotension include those with the following conditions or characteristics: heart failure with systolic blood pressure below 100 mmHg, ischemic heart disease, cerebrovascular disease, hyponatremia, high dose diuretic therapy, renal dialysis, or severe volume and/or salt depletion of any etiology.

In these patients, enalapril maleate should be started under very close medical supervision and such patients should be followed closely for the first two weeks of treatment and whenever the dose of enalapril maleate and/or diuretic is increased.

Symptomatic hypotension is also possible in patients with severe aortic stenosis or hypertrophic cardiomyopathy.

Surgery/Anesthesia

In patients undergoing major surgery or during anesthesia with agents that produce hypotension, enalapril maleate may block angiotensin II formation secondary to compensatory renin release. If hypotension occurs and is considered to be through this mechanism, it can be corrected by volume expansion.

5.4 Hepatic Failure

Rarely, ACE inhibitors have been associated with a syndrome that starts with cholestatic jaundice and progresses to fulminant hepatic necrosis, and (sometimes) death. The mechanism of this syndrome is not understood. Patients receiving ACE inhibitors who develop jaundice or marked elevations of hepatic enzymes should discontinue the ACE inhibitor and receive appropriate medical follow-up.

5.5 Impaired Renal Function

Monitor renal function in patients treated with enalapril maleate. Changes in renal function including acute renal failure can be caused by drugs that inhibit the renin-angiotensin system. Patients whose renal function may depend in part on the activity of the renin-angiotensin system (e.g., patients with renal artery stenosis, chronic kidney disease, severe congestive heart failure, post-myocardial infarction or volume depletion) may be at particular risk of developing acute renal failure on enalapril maleate. Consider withholding or discontinuing therapy in patients who develop a clinically significant decrease in renal function on enalapril maleate [see Adverse Reactions (6.2) and Drug Interactions (7.2, 7.3)].

5.6 Hyperkalemia

Serum potassium should be monitored in patients receiving enalapril maleate. Drugs that inhibit the renin angiotensin system can cause hyperkalemia. Risk factors for the development of hyperkalemia include renal insufficiency, diabetes mellitus, and the concomitant use of potassium-sparing diuretics, potassium supplements and/or potassium-containing salt substitutes [see Drug Interactions (7.3)].

6 ADVERSE REACTIONS

The following adverse reactions are described elsewhere:

- Angioedema [see Warnings and Precautions (5.2)]
- Hypotension [see Warnings and Precautions (5.3)]
- Hepatic failure [see Warnings and Precautions (5.4)]
- Renal impairment [see Warnings and Precautions (5.5)]
- Hyperkalemia [see Warnings and Precautions (5.6)]

6.1 Clinical Trials Experience

Because clinical trials are conducted under widely varying conditions, adverse reaction rates observed in clinical trials of a drug cannot be directly compared to rates in the clinical trials of another drug and may not reflect the rates observed in clinical practice.

Enalapril has been evaluated for safety in more than 10,000 patients, including over 1,000 patients treated for one year or more.

In clinical trials, discontinuation of therapy for clinical adverse experiences was required in 3.3% of patients with hypertension and in 5.7% of patients with heart failure.

Hypertension

Adverse reactions (where rate on enalapril exceeds the rate on placebo by at least 0.2%) occurring in greater than 1% of patients with hypertension treated with enalapril in controlled clinical trials are shown below. In patients treated with enalapril, the maximum duration of therapy was three years; in placebo treated patients, the maximum duration of therapy was 12 weeks.

Adverse Reactions Occurring in Greater Than 1% of Patients With Hypertension
 | Enalapril Maleate Tablets (n = 2314) Incidence (discontinuation) | Placebo (n = 230) Incidence
Body As A Whole
Fatigue | 3.0 (<0.1) | 2.6
Orthostatic Effects | 1.2 (<0.1) | 0.0
Asthenia | 1.1 (0.1) | 0.9
Respiratory
Cough | 1.3 (0.1) | 0.9
Skin
Rash | 1.4 (0.4) | 0.4

Heart Failure

Adverse reactions seen in clinical trials of heart failure were similar to those seen in clinical trials for hypertension. In patients treated for heart failure, there was an increased incidence of hypotension 6.7 percent versus 0.6 percent in placebo and dizziness 7.9 percent versus 0.6 percent in placebo.

6.2 Other Adverse Reactions from Clinical Studies or Postmarketing Experience

The following adverse reactions have been reported in clinical studies or postmarketing experience with enalapril. Because some of these reactions were reported voluntarily from a population of uncertain size, it is not always possible to reliably estimate their frequency or establish a causal relationship to drug exposure.

Other serious clinical adverse experiences occurring since the drug was marketed or adverse experiences occurring in 0.5 to 1.0% of patients with hypertension or heart failure in clinical trials are listed below and, within each category, are in order of decreasing severity.

Cardiovascular:Cardiac arrest; myocardial infarction or cerebrovascular accident, possibly secondary to excessive hypotension in high risk patients [see Warnings and Precautions (5.3)] ; pulmonary embolism and infarction; pulmonary edema; rhythm disturbances, including atrial tachycardia and bradycardia; atrial fibrillation; palpitation; Raynaud's phenomenon.

Digestive:Ileus, pancreatitis, melena, anorexia, dyspepsia, constipation, glossitis, stomatitis, dry mouth.

Hematologic:Rare cases of neutropenia, thrombocytopenia, and bone marrow depression.

Musculoskeletal:Muscle cramps.

Nervous/Psychiatric:Depression, confusion, ataxia, somnolence, insomnia, nervousness, peripheral neuropathy (e.g., paresthesia, dysesthesia), dream abnormality.

Respiratory:Bronchospasm, rhinorrhea, sore throat and hoarseness, asthma, upper respiratory infection, pulmonary infiltrates, eosinophilic pneumonitis.

Skin:Exfoliative dermatitis, toxic epidermal necrolysis, Stevens-Johnson syndrome, pemphigus, herpes zoster, erythema multiforme, urticaria, pruritus, alopecia, flushing, diaphoresis, photosensitivity.

Special Senses:Blurred vision, taste alteration, anosmia, tinnitus, conjunctivitis, dry eyes, tearing.

Urogenital:Flank pain, gynecomastia, impotence.

Miscellaneous:A symptom complex has been reported which may include some or all of the following: a positive ANA, an elevated erythrocyte sedimentation rate, arthralgia/arthritis, myalgia/myositis, fever, serositis, vasculitis, leukocytosis, eosinophilia, photosensitivity, dermatologic manifestations.

7 DRUG INTERACTIONS

7.1 Non-Steroidal Anti-Inflammatory Agents (NSAIDs) Including Selective Cyclooxygenase-2 Inhibitors (COX-2 Inhibitors)

In patients who are elderly, volume-depleted (including those on diuretic therapy), or with compromised renal function, co-administration of NSAIDs, including selective COX-2 inhibitors, with ACE inhibitors, including enalapril, may result in deterioration of renal function, including possible acute renal failure. These effects are usually reversible. Monitor renal function periodically in patients receiving enalapril and NSAID therapy.

In a clinical pharmacology study, indomethacin or sulindac was administered to hypertensive patients receiving enalapril maleate. In this study, there was no evidence of a blunting of the antihypertensive action of enalapril maleate. However, reports suggest that NSAIDs may diminish the antihypertensive effect of ACE inhibitors.

7.2 Dual Blockade of the Renin-Angiotensin System (RAS)

Dual blockade of the RAS with angiotensin receptor blockers, ACE inhibitors, or aliskiren is associated with increased risks of hypotension, hyperkalemia, and changes in renal function (including acute renal failure) compared to monotherapy. In most patients no benefit has been associated with using two RAS inhibitors concomitantly. In general, avoid combined use of RAS inhibitors. Closely monitor blood pressure, renal function and electrolytes in patients on enalapril maleate and other agents that affect the RAS.

Do not co-administer aliskiren with enalapril maleate in patients with diabetes. Avoid use of aliskiren with enalapril maleate in patients with renal impairment (GFR <60 mL/min).

7.3 Agents Increasing Serum Potassium

Enalapril maleate attenuates potassium loss caused by thiazide-type diuretics. Potassium-sparing diuretics (e.g., spironolactone, triamterene, or amiloride), potassium supplements, or potassium-containing salt substitutes may lead to significant increases in serum potassium.

7.4 Lithium

Lithium toxicity has been reported in patients receiving enalapril and lithium concomitantly which was generally reversible. It is recommended that serum lithium levels be monitored frequently if enalapril is administered concomitantly with lithium.

7.5 Gold

Nitritoid reactions (symptoms include facial flushing, nausea, vomiting, and hypotension) have been reported rarely in patients on therapy with injectable gold (sodium aurothiomalate) and concomitant ACE inhibitor therapy including enalapril.

7.6 mTOR Inhibitors

Patients taking concomitant mTOR inhibitor (e.g., temsirolimus, sirolimus, everolimus) therapy may be at increased risk for angioedema [ see Warnings and Precautions (5.2)].

7.7 Neprilysin Inhibitor

Patients taking concomitant neprilysin inhibitors may be at increased risk for angioedema [see Warnings and Precautions (5.2)] .

8 USE IN SPECIFIC POPULATIONS

8.1 Pregnancy

Risk Summary

Enalapril maleate can cause fetal harm when administered to a pregnant woman. Use of drugs that act on the renin-angiotensin system during the second and third trimesters of pregnancy reduces fetal renal function and increases fetal and neonatal morbidity and death. Most epidemiologic studies examining fetal abnormalities after exposure to antihypertensive use in the first trimester have not distinguished drugs affecting the renin-angiotensin system from other antihypertensive agents. When pregnancy is detected, discontinue enalapril maleate as soon as possible.

The estimated background risk of major birth defects and miscarriage for the indicated population(s) are unknown. In the general U.S. population, the estimated background risk of major birth defects and miscarriage in clinically recognized pregnancies is 2-4% and 15-20%, respectively.

Clinical Considerations

Disease-associated maternal and/or embryo/fetal risk Hypertension in pregnancy increases the maternal risk for pre-eclampsia, gestational diabetes, premature delivery, and delivery complications (e.g., need for cesarean section, and post-partum hemorrhage). Hypertension increases the fetal risk for intrauterine growth restriction and intrauterine death. Pregnant women with hypertension should be carefully monitored and managed accordingly. Adverse reactions in the fetus or in neonates with a history of in utero exposure to enalapril maleate. Use of drugs that act on the renin-angiotensin system during the second and third trimesters of pregnancy can result in the following: reduced fetal renal function leading to anuria and renal failure, oligohydramnios, fetal lung hypoplasia, skeletal deformations, including skull hypoplasia, hypotension, and death. In the unusual case that there is no appropriate alternative to therapy with drugs affecting the renin-angiotensin system for a particular patient, apprise the mother of the potential risk to the fetus. Perform serial ultrasound examinations to assess the intra-amniotic environment. Fetal testing may be appropriate, based on the week of pregnancy. Patients and physicians should be aware, however, that oligohydraminos may not appear until after the fetus has sustained irreversible injury. Closely observe infants with histories of in utero exposure to enalapril maleate for hypotension, oliguria, and hyperkalemia. If oliguria or hypotension occurs in neonates with a history of in utero exposure to enalapril maleate, support blood pressure and renal perfusion. Exchange transfusions or dialysis may be required as a means of reversing hypotension and substituting for disordered renal function.

8.2 Lactation

Risk Summary

Enalapril and enalaprilat have been detected in human breast milk. Because of the potential for severe adverse reactions in the breastfed infant, including hypotension, hyperkalemia and renal impairment, advise women not to breastfeed during treatment with enalapril maleate.

8.4 Pediatric Use

Neonates with a history of in utero exposure to enalapril maleate

If oliguria or hypotension occurs, direct attention toward support of blood pressure and renal perfusion. Exchange transfusions or dialysis may be required as a means of reversing hypotension and/or substituting for disordered renal function. Enalapril, which crosses the placenta, has been removed from neonatal circulation by peritoneal dialysis with some clinical benefit, and theoretically may be removed by exchange transfusion, although there is no experience with the latter procedure.

Pediatric patients with hypertension

Enalapril maleate is not recommended in neonates (i.e., infants 1 month of age or less), preterm infants who have not reached a corrected post-conceptual age of 44 weeks, and in pediatric patients with glomerular filtration rate <30 mL/min/1.73 m^2 [see Nonclinical Toxicology (13.2)].

Enalapril lowers blood pressure in hypertensive pediatric patients age 6 years to 16 years. Use of enalapril in these age groups is supported by evidence from adequate and well-controlled studies of enalapril in pediatric and adult patients as well as by published literature in pediatric patients [see Clinical Pharmacology (12.3) and Dosage and Administration (2.1)] . Clinical efficacy studies of enalapril in pediatric patients with hypertension did not enroll patients less than 6 years of age. In a previous clinical study in pediatric patients between 2 months and 6 years of age, a higher weight-based dose was required to match exposure in children aged 6 to 16 years [see Clinical Pharmacology (12.3)] .

It is unknown whether post-natal use of ACE inhibitors such as enalapril before maturation of renal function is complete has long-term deleterious effects on the kidney. In humans, nephrogenesis is thought to be complete around birth; however maturation of other aspects of kidney function (such as glomerular filtration and tubular function) may continue until approximately 2 years of age [see Nonclinical Toxicology (13.2)].

Pediatric patients with heart failure or asymptomatic left ventricular dysfunction

Safety and effectiveness of enalapril have not been established in pediatric patients with heart failure or asymptomatic left ventricular dysfunction.

8.5 Geriatric Use

This drug is known to be substantially excreted by the kidney, and the risk of adverse reactions to this drug may be greater in patients with impaired renal function. Because elderly patients are more likely to have decreased renal function, care should be taken in dose selection, and it may be useful to monitor renal function.

8.6 Race

ACE inhibitors, including enalapril maleate, as monotherapy have an effect on blood pressure that is less in Black patients than in non-Blacks.

8.7 Renal Impairment

Use a lower initial dose of enalapril maleate in patients undergoing hemodialysis and in patients whose eGFR is ≤ 30 mL/min [see Dosage and Administration (2.1) and Clinical Pharmacology (12.3)].

10 OVERDOSAGE

Limited data are available in regard to overdosage in humans. Single oral doses of enalapril above 1,000 mg/kg and ≥1,775 mg/kg were associated with lethality in mice and rats, respectively. The most likely manifestation of overdosage would be hypotension, for which the usual treatment would be intravenous infusion of normal saline solution. Enalaprilat may be removed from general circulation by hemodialysis and has been removed from neonatal circulation by peritoneal dialysis.

11 DESCRIPTION

Enalapril maleate oral solution is the maleate salt of enalapril, the ethyl ester prodrug of a long-acting angiotensin-converting enzyme inhibitor, enalaprilat. Enalapril maleate is chemically described as (S)-1-[N-[1-(ethoxycarbonyl)-3-phenylpropyl]-L-alanyl]-L-proline, (Z)-2-butenedioate salt (1:1). Its empirical formula is C20H28N2O5•C4H4O4, and its structural formula is:

Enalapril maleate is a white to off-white, crystalline powder with a molecular weight of 492.52. It is sparingly soluble in water, soluble in ethanol, and freely soluble in methanol. Enalapril maleate oral solution is a ready-to-use oral solution. Each 1 mL contains 1 mg of enalapril maleate, USP equivalent to 0.764 mg of enalapril. Inactive ingredients include citric acid, mixed berry flavor, purified water, sodium benzoate, sodium citrate, and sucralose. It may also contain hydrochloric acid or sodium hydroxide for pH adjustment. Enalapril maleate oral solution is clear and colorless.

12 CLINICAL PHARMACOLOGY

12.1 Mechanism of Action

Enalapril, after hydrolysis to enalaprilat, inhibits angiotensin-converting enzyme (ACE) in human subjects and animals. ACE is a peptidyl dipeptidase that catalyzes the conversion of angiotensin I to the vasoconstrictor substance, angiotensin II. Angiotensin II also stimulates aldosterone secretion by the adrenal cortex. The beneficial effects of enalapril in hypertension and heart failure appear to result primarily from suppression of the renin-angiotensin-aldosterone system. Inhibition of ACE results in decreased plasma angiotensin II, which leads to decreased vasopressor activity and to decreased aldosterone secretion. Although the latter decrease is small, it results in small increases of serum potassium. In hypertensive patients treated with enalapril maleate tablets alone for up to 48 weeks, mean increases in serum potassium of approximately 0.2 mEq/L were observed. In patients treated with enalapril maleate tablets plus a thiazide diuretic, there was essentially no change in serum potassium [see Warnings and Precautions (5.6)] . Removal of angiotensin II negative feedback on renin secretion leads to increased plasma renin activity.

ACE is identical to kininase, an enzyme that degrades bradykinin. Whether increased levels of bradykinin, a potent vasodepressor peptide, play a role in the therapeutic effects of enalapril maleate remains to be elucidated.

While the mechanism through which enalapril maleate lowers blood pressure is believed to be primarily suppression of the renin-angiotensin-aldosterone system, enalapril is antihypertensive even in patients with low-renin hypertension. Although enalapril maleate tablets were antihypertensive in all races studied, Black hypertensive patients (usually a low-renin hypertensive population) had a smaller average response to enalapril monotherapy than non-Black patients.

12.2 Pharmacodynamics

Hypertension

Adults

Administration of enalapril maleate tablets to patients with hypertension of severity ranging from mild to severe results in a reduction of both supine and standing blood pressure, usually with no orthostatic component. Symptomatic postural hypotension is therefore infrequent, although it might be anticipated in volume-depleted patients [see Warnings and Precautions (5.3)] .

In most patients studied, after oral administration of a single dose of enalapril, onset of antihypertensive activity was seen at one hour with peak reduction of blood pressure achieved by four to six hours.

At recommended doses, antihypertensive effects have been maintained for at least 24 hours. In some patients the effects may diminish toward the end of the dosing interval [see Dosageand Administration (2.1)] .

In some patients achievement of optimal blood pressure reduction may require several weeks of therapy.

The antihypertensive effects of enalapril have continued during long-term therapy. Abrupt withdrawal of enalapril has not been associated with a rapid increase in blood pressure.

In hemodynamic studies in patients with essential hypertension, blood pressure reduction was accompanied by a reduction in peripheral arterial resistance with an increase in cardiac output and little or no change in heart rate. Following administration of enalapril, there is an increase in renal blood flow; glomerular filtration rate is usually unchanged. The effects appear to be similar in patients with renovascular hypertension.

When given together with thiazide-type diuretics, the blood pressure lowering effects of enalapril maleate are approximately additive.

In a clinical pharmacology study, indomethacin or sulindac was administered to hypertensive patients receiving enalapril maleate tablets. In this study, there was no evidence of a blunting of the antihypertensive action of enalapril [see Drug Interactions (7.1)] .

Pediatric Patients

In a clinical study involving 110 hypertensive pediatric patients 6 to 16 years of age, patients who weighed <50 kg received either 0.625, 2.5, or 20 mg of enalapril daily and patients who weighed ≥50 kg received either 1.25, 5, or 40 mg of enalapril daily. Enalapril administration once daily lowered trough blood pressure in a dose-dependent manner. The dose-dependent antihypertensive efficacy of enalapril was consistent across all subgroups (age, Tanner stage, gender, race). However, the lowest doses studied, 0.625 mg and 1.25 mg, corresponding to an average of 0.02 mg/kg once daily, did not appear to offer consistent antihypertensive efficacy. In this study, enalapril maleate was generally well tolerated. Limited information exists on the blood pressure lowering effects in pediatric patients less than 6 years of age.

Heart Failure

In trials in patients treated with digitalis and diuretics, treatment with enalapril resulted in decreased systemic vascular resistance, blood pressure, pulmonary capillary wedge pressure and heart size, and increased cardiac output and exercise tolerance. Heart rate was unchanged or slightly reduced, and mean ejection fraction was unchanged or increased. There was a beneficial effect on severity of heart failure as measured by the New York Heart Association (NYHA) classification and on symptoms of dyspnea and fatigue. Hemodynamic effects were observed after the first dose, and appeared to be maintained in uncontrolled studies lasting as long as four months. Effects on exercise tolerance, heart size, and severity and symptoms of heart failure were observed in placebo-controlled studies lasting from eight weeks to over one year.

12.3 Pharmacokinetics

The pharmacokinetics of ready-to-use enalapril maleate oral solution was shown to be bioequivalent to that of reconstituted enalapril maleate powder for oral solution under fasted conditions.

Reconstituted enalapril maleate powder for oral solution was shown to be bioequivalent to Vasotec®tablets. Reconstituted enalapril maleate powder for oral solution was also evaluated under fed and fasted conditions. A high-fat meal reduced the Cmaxof enalapril and enalaprilat by 46% and 36%, respectively. The exposure, as measured by AUC, to enalaprilat was reduced by 23%.

The time to peak concentrations (Cmax) was delayed by 20 minutes for enalapril and 62 minutes for enalaprilat. The trough plasma concentrations of enalapril (from 6 to 12 hours) and enalaprilat (from 16 to 36 hours) are similar between fasted and fed administrations.

Adults

Following oral administration of enalapril maleate tablets, peak serum concentrations of enalapril occur within about one hour. Based on urinary recovery, the extent of absorption of enalapril is approximately 60%. Enalapril absorption is not influenced by the presence of food in the gastrointestinal tract. Following absorption, enalapril is hydrolyzed to enalaprilat, which is a more potent angiotensin-converting enzyme inhibitor than enalapril; enalaprilat is poorly absorbed when administered orally. Peak serum concentrations of enalaprilat occur three to four hours after an oral dose of enalapril maleate. Excretion of enalapril is primarily renal.

Approximately 94% of the dose is recovered in the urine and feces as enalaprilat or enalapril. The principal components in urine are enalaprilat, accounting for about 40% of the dose, and intact enalapril. There is no evidence of metabolites of enalapril, other than enalaprilat.

The serum concentration profile of enalaprilat exhibits a prolonged terminal phase, apparently representing a small fraction of the administered dose that has been bound to ACE. The amount bound does not increase with dose, indicating a saturable site of binding. The effective half-life for accumulation of enalaprilat following multiple doses of enalapril maleate is 11 hours.

The disposition of enalapril and enalaprilat in patients with renal insufficiency is similar to that in patients with normal renal function until the glomerular filtration rate is 30 mL/min or less. With glomerular filtration rate ≤30 mL/min, peak and trough enalaprilat levels increase, time to peak concentration increases, and time to steady state may be delayed. The effective half-life of enalaprilat following multiple doses of enalapril maleate is prolonged at this level of renal insufficiency [ see Dosage and Administration (2.1)]. Enalaprilat is dialyzable at the rate of 62 mL/min. Administering enalapril 1 h after hemodialysis led to a reduction of approximately 50% in the enalaprilat AUC0-6 hcompared to off dialysis days.

Pediatric Patients

A multiple dose pharmacokinetics study was conducted in 40 hypertensive male and female pediatric patients aged 2 months to ≤16 years following daily oral administration of 0.07 to 0.14 mg/kg enalapril maleate. At steady state, the mean effective half-life for accumulation of enalaprilat was 14 hours and the mean urinary recovery of total enalapril and enalaprilat in 24 hours was 68% of the administered dose. Conversion of enalapril to enalaprilat was in the range of 63-76%. The overall results of this study indicate that the pharmacokinetics of enalapril in hypertensive children aged 6 to ≤16 years are consistent across the studied age groups and consistent with pharmacokinetic historical data in healthy adults. Hypertensive children aged 2 months to 6 years required higher weight-based doses (0.13 mg/kg and 0.11 mg/kg) compared to the older age groups (0.11 mg/kg and 0.07 mg/kg), to achieve similar steady-state AUC.

In the above pediatric study, enalapril maleate was given as tablets and for those children and infants who were unable to swallow tablets or who required a lower dose than is available in tablet form, enalapril was administered in a suspension formulation.

13 NONCLINICAL TOXICOLOGY

13.1 Carcinogenesis, Mutagenesis, Impairment of Fertility

There was no evidence of a tumorigenic effect when enalapril was administered for 106 weeks to male and female rats at doses up to 90 mg/kg/day or for 94 weeks to male and female mice at doses up to 90 and 180 mg/kg/day, respectively. These doses are 26 times (in rats and female mice) and 13 times (in male mice) the maximum recommended human daily dose (MRHDD) when compared on a body surface area basis.

Neither enalapril maleate nor the active diacid was mutagenic in the Ames microbial mutagen test with or without metabolic activation. Enalapril was also negative in the following genotoxicity studies: rec-assay, reverse mutation assay with E. coli, sister chromatid exchange with cultured mammalian cells, and the micronucleus test with mice, as well as in an in vivocytogenic study using mouse bone marrow.

There were no adverse effects on reproductive performance of male and female rats treated with up to 90 mg/kg/day of enalapril (26 times the MRHDD when compared on a body surface area basis).

13.2 Animal Toxicology and/or Pharmacology

In several experimental published studies, rat pups exposed to daily enalapril from birth to post‑natal Day 13 (the period of nephrogenesis in this species) developed irreversible renal toxicity. In contrast, treatment after post-natal Day 14 was not toxic to the more mature kidney. Rat kidney development at birth and at 14 days is similar to the human at mid-trimester and in infancy, respectively. The toxic dosages in these studies were about 10X, on a mg/m^2basis, the highest recommended oral (0.58 mg/kg/day) pediatric dosages to treat hypertension. Lower dosages were not studied.

14 CLINICAL STUDIES

14.1 Heart Failure, Mortality Trials

In a multicenter, placebo-controlled clinical trial, 2,569 patients with all degrees of symptomatic heart failure and ejection fraction ≤35 percent were randomized to placebo or enalapril and followed for up to 55 months (SOLVD-Treatment). Use of enalapril was associated with an 11 percent reduction in all-cause mortality and a 30 percent reduction in hospitalization for heart failure. Diseases that excluded patients from enrollment in the study included severe stable angina (>2 attacks/day), hemodynamically significant valvular or outflow tract obstruction, renal failure (creatinine >2.5 mg/dL), cerebral vascular disease (e.g., significant carotid artery disease), advanced pulmonary disease, malignancies, active myocarditis and constrictive pericarditis. The mortality benefit associated with enalapril does not appear to depend upon digitalis being present.

A second multicenter trial used the SOLVD protocol for study of asymptomatic or minimally symptomatic patients. SOLVD-Prevention patients, who had left ventricular ejection fraction ≤35% and no history of symptomatic heart failure, were randomized to placebo (n = 2117) or enalapril (n = 2111) and followed for up to 5 years. The majority of patients in the SOLVD-Prevention trial had a history of ischemic heart disease. A history of myocardial infarction was present in 80 percent of patients, current angina pectoris in 34 percent, and a history of hypertension in 37 percent. No statistically significant mortality effect was demonstrated in this population. Enalapril-treated subjects had 32% fewer first hospitalizations for heart failure, and 32% fewer total heart failure hospitalizations. Compared to placebo, 32 percent fewer patients receiving enalapril developed symptoms of overt heart failure. Hospitalizations for cardiovascular reasons were also reduced. There was an insignificant reduction in hospitalizations for any cause in the enalapril treatment group (for enalapril vs. placebo, respectively, 1166 vs. 1201 first hospitalizations, 2649 vs. 2840 total hospitalizations), although the study was not powered to look for such an effect.

The SOLVD-Prevention trial was not designed to determine whether treatment of asymptomatic patients with low ejection fraction would be superior, with respect to preventing hospitalization, to closer follow-up and use of enalapril at the earliest sign of heart failure. However, under the conditions of follow-up in the SOLVD-Prevention trial (every 4 months at the study clinic; personal physician as needed), 68% of patients on placebo who were hospitalized for heart failure had no prior symptoms recorded which would have signaled initiation of treatment.

The SOLVD-Prevention trial was also not designed to show whether enalapril modified the progression of underlying heart disease.

In another multicenter, placebo-controlled trial (CONSENSUS) limited to patients with NYHA Class IV congestive heart failure and radiographic evidence of cardiomegaly, use of enalapril was associated with improved survival. The results are shown in the following table.

CONSENSUS Survival Rates
 | SURVIVAL (%)
 | Six Months | One Year
VASOTEC (n = 127) | 74 | 64
Placebo (n = 126) | 56 | 48

In both CONSENSUS and SOLVD-Treatment trials, patients were also usually receiving digitalis, diuretics or both.

16 HOW SUPPLIED/STORAGE AND HANDLING

Enalapril maleate oral solution is a ready-to-use solution that contains 1 mg/mL of enalapril maleate. It is a clear, colorless oral solution with a mixed berry flavor, packaged in a 150-mL, white, round, high-density polyethylene bottle with a white, polypropylene, child-resistant cap and tamper-evident seal. Each bottle contains 150 mL.

NDC 52536-401-01

Store refrigerated (2°C-8°C/36°F-46°F) in a tightly closed container. Patients may store enalapril maleate either refrigerated (2°C-8°C/36°F-46°F) or at room temperature (20°C-25°C/68°F-77°F). If stored at room temperature, discard after 60 days. Avoid freezing and excessive heat.

17 PATIENT COUNSELING INFORMATION

•Pregnancy

Tell female patients of childbearing age about the consequences of exposure to enalapril maleate during pregnancy. Discuss treatment options with women planning to become pregnant. Patients should be asked to report pregnancies to their physicians as soon as possible.

•Angioedema

Angioedema, including laryngeal edema, may occur at any time during treatment with angiotensin-converting enzyme inhibitors, including enalapril. Advise patients to report immediately any signs or symptoms suggesting angioedema (swelling of face, extremities, eyes, lips, or tongue, or difficulty in swallowing or breathing) and to consult with the prescribing physician before taking more drug.

•Hypotension

Caution patients to report lightheadedness, especially during the first few days of therapy. If actual syncope occurs, tell patients to discontinue the drug until they have consulted with the prescribing physician.

Tell patients that excessive perspiration and dehydration may lead to an excessive fall in blood pressure because of reduction in fluid volume. Other causes of volume depletion such as vomiting or diarrhea may also lead to a fall in blood pressure; advise patients to consult with their physician.

•Hyperkalemia

Tell patients to consult their physician prior to using salt substitutes containing potassium.

Manufactured for:
Wilshire Pharmaceuticals, Inc.
Atlanta, GA 30328 USA

PI-00789 Rev.00 Sep 2023

PRINCIPAL DISPLAY PANEL - Bottle Label

Bottle Label

NDC 52536-401-01

Enalapril maleate

Oral Solution
1 mg/mL

For Oral Use Only

READY TO USE

150 mL

Wilshire Pharmaceuticals, Inc.

Rx Only

Each 1 mL contains 1 mg
enalapril maleate equivalent
to 0.764 mg enalapril.

Usual Dose:See prescribing information.

Store refrigerated
2° - 8°C (36° - 46°F)

Patients may store Enalapril Maleate Oral Solution at room temperature (20°-25°C/68°-77°F).
If stored at room temperature,discard after 60 days.
Avoid freezing and excessive heat.
Keep container tightly closed.

KEEP THIS AND ALL MEDICATIONS OUT OF THE
REACH OF CHILDREN

LBL-00790 Rev.00 Sep2023

Manufactured for:
Wilshire Pharmaceuticals, Inc.
Wilmington, MA 01887 USA

Lot:
Exp: